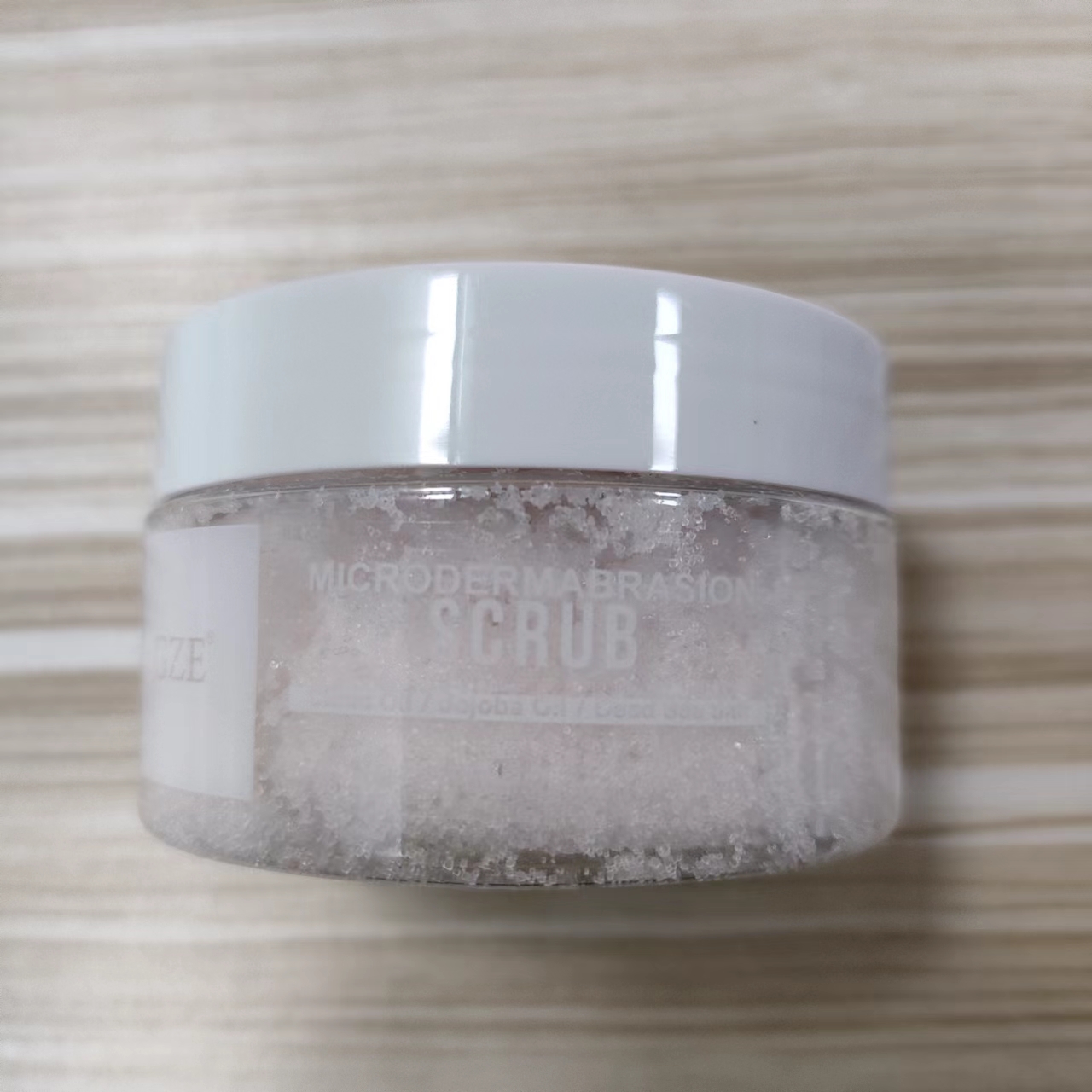 DRUG LABEL: GZE MICRODERMABRASION SCRUB
NDC: 74458-214 | Form: GRANULE
Manufacturer: Guangzhou Yilong Cosmetics Co., Ltd
Category: otc | Type: HUMAN OTC DRUG LABEL
Date: 20241121

ACTIVE INGREDIENTS: SEA SALT 15 g/100 g; SIMMONDSIA CHINENSIS (JOJOBA) SEED OIL 15 g/100 g
INACTIVE INGREDIENTS: GLYCERIN; CITRUS AURANTIFOLIA (LIME) OIL; CITRUS AURANTIUM DULCIS (ORANGE) OIL; ETHYLHEXYLGLYCERIN; AQUA; CITRUS LIMON (LEMON) PEEL OIL

GZE MICRODERMABRASION SCRUB

ACTIVE INGREDIENT

Simmondsia Chinensis (Jojoba) Seed Oil

Sea Salt

INDICATIONS AND USAGE

Apply onto wet or dry skin and scrub
desired areas in an upward motion. Massage gently but firmly for
approximately 3 minutes and rinse.

PURPOSE

Exfoliating

WARNINGS

For external use only.

Stop use and ask a doctor if rash occurs.

Do not use on damaged or broken skin.

When using this product keep out of eyes. Rinse with water to remove.

Keep out of reach of children. If swallowed, get medical help or contact a Poison Control Center right away.